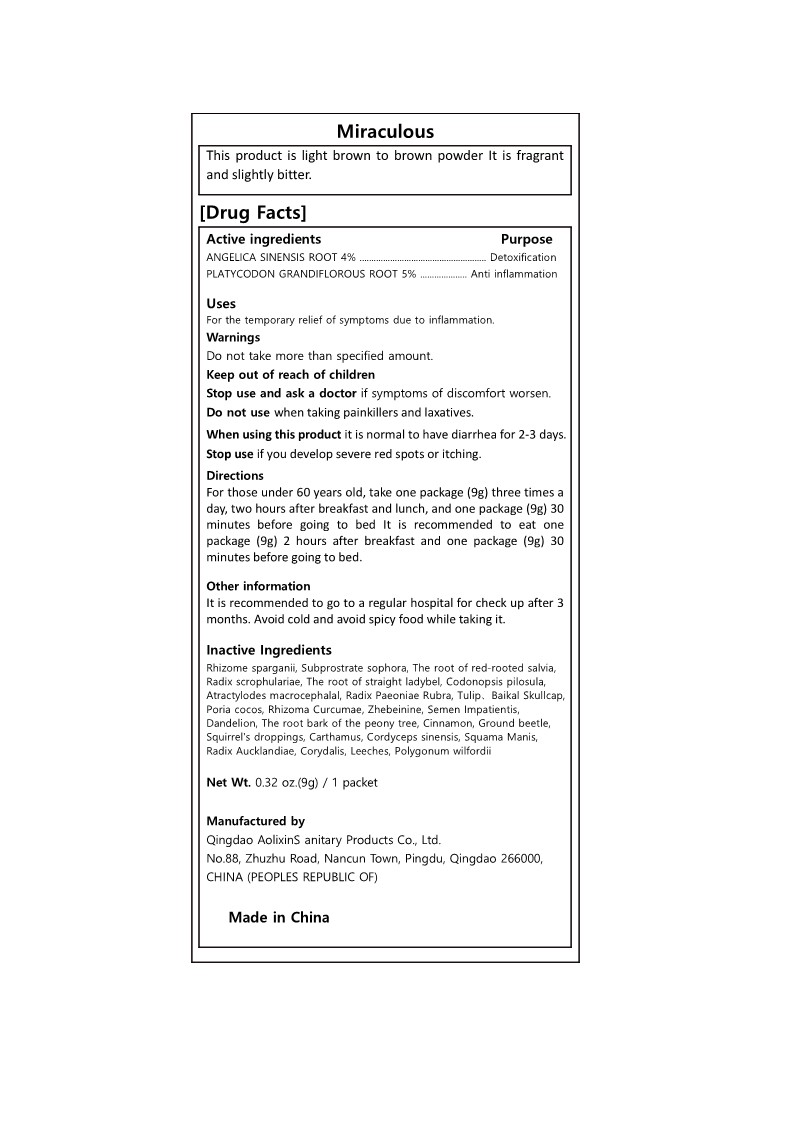 DRUG LABEL: Miraculous
NDC: 82672-302 | Form: POWDER
Manufacturer: Qingdao Aolixin Sanitary Products Co., Ltd.
Category: homeopathic | Type: HUMAN OTC DRUG LABEL
Date: 20220417

ACTIVE INGREDIENTS: ANGELICA SINENSIS ROOT 4 g/100 g; PLATYCODON GRANDIFLORUS ROOT 5 g/100 g
INACTIVE INGREDIENTS: SCROPHULARIA NINGPOENSIS ROOT; ADENOPHORA STRICTA ROOT; SCUTELLARIA BAICALENSIS WHOLE; IMPATIENS BALSAMINA SEED; SPARGANIUM STOLONIFERUM ROOT; SALVIA MILTIORRHIZA ROOT; ATRACTYLODES MACROCEPHALA ROOT; MANIS PENTADACTYLA SCALE; SOPHORA TONKINENSIS WHOLE; CODONOPSIS PILOSULA ROOT; CARTHAMUS TINCTORIUS WHOLE; DICENTRA CANADENSIS ROOT; REYNOUTRIA MULTIFLORA WHOLE; TURMERIC; FRITILLARIA THUNBERGII WHOLE; TARAXACUM OFFICINALE; PAEONIA X SUFFRUTICOSA ROOT; CINNAMON; EUPOLYPHAGA SINENSIS; OPHIOCORDYCEPS SINENSIS; DOLOMIAEA COSTUS ROOT; PAEONIA LACTIFLORA ROOT; WOLFIPORIA COCOS WHOLE

Miraculous

Active Ingredients

ANGELICA SINENSIS ROOT 4%

PLATYCODON GRANDIFLOROUS ROOT 5%

PURPOSE

Detoxification

Anti inflammation

Uses

For the temporary relief of symptoms due to inflammation.

Warnings

Do not take more than specified amount.

Warnings

Keep out of reach of children

Stop use and ask a doctor

if symptoms of discomfort worsen.

if you develop severe red spots or itching.

Do not use

when taking painkillers and laxatives.

When using

it is normal to have diarrhea for 2-3 days.

Directions

For those under 60 years old, take one package (9g) three times a day, two hours after breakfast and lunch, and one package (9g) 30 minutes before going to bed It is recommended to eat one package (9g) 2 hours after breakfast and one package (9g) 30 minutes before going to bed.

Other Information

It is recommended to go to a regular hospital for check up after 3 months. Avoid cold and avoid spicy food while taking it.

Inactive Ingredients

Rhizome sparganii, Subprostrate sophora, The root of red-rooted salvia, Radix scrophulariae, The root of straight ladybel, Codonopsis pilosula, Atractylodes macrocephalal, Radix Paeoniae Rubra, Tulip、Baikal Skullcap, Poria cocos, Rhizoma Curcumae, Zhebeinine, Semen Impatientis, Dandelion, The root bark of the peony tree, Cinnamon, Ground beetle, Squirrel's droppings, Carthamus, Cordyceps sinensis, Squama Manis, Radix Aucklandiae, Corydalis, Leeches, Polygonum wilfordii